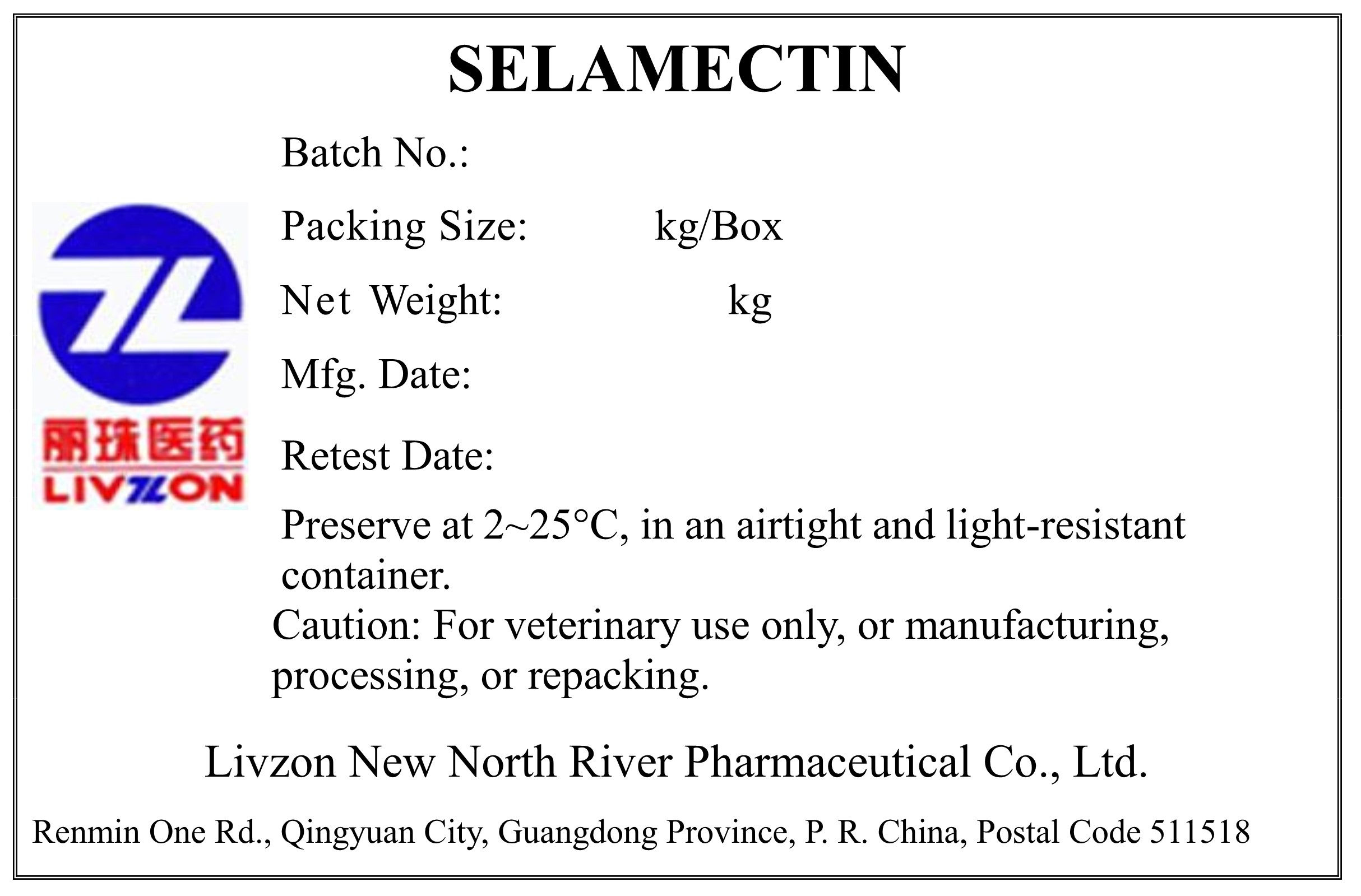 DRUG LABEL: Selamectin
NDC: 20076-0000 | Form: POWDER
Manufacturer: Livzon New North River Pharmaceutical Co., Ltd.
Category: other | Type: BULK INGREDIENT - ANIMAL DRUG
Date: 20241224

ACTIVE INGREDIENTS: SELAMECTIN 1 kg/1 kg

Selamectin